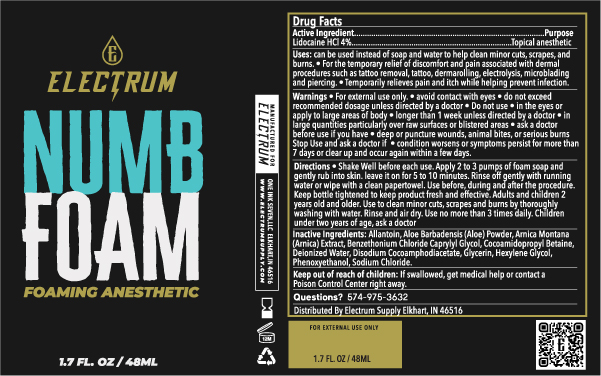 DRUG LABEL: Electrum Numb Foam
NDC: 76348-596 | Form: SOAP
Manufacturer: RENU LABORATORIES, LLC
Category: otc | Type: HUMAN OTC DRUG LABEL
Date: 20250425

ACTIVE INGREDIENTS: LIDOCAINE HYDROCHLORIDE 1.92 g/48 mL
INACTIVE INGREDIENTS: WATER; HEXYLENE GLYCOL; SODIUM CHLORIDE; ALLANTOIN; ALOE VERA LEAF; PHENOXYETHANOL; ARNICA MONTANA; CAPRYLYL GLYCOL; DISODIUM COCOAMPHODIACETATE; GLYCERIN; BENZETHONIUM CHLORIDE; COCAMIDOPROPYL BETAINE

Electrum Numb Foam

Uses

can be used instead of soap and water to help clean minor cuts, scrapes, and burns.

- For the temporary relief of discomfort and pain associated with dermal procedures such as tattoo removal, tattoo, dermarolling, electrolysis, microblading and piercing.
- Temporarily relieves pain and itch while helping prevent infection

Directions

- Shake Well before each use. Apply 2 to 3 pumps of foam soap and gently rub into skin. Leave it on for 5 to 10 minutes. Rinse off gently with running water or wipe with a clean paper towel. Use before, during and after the procedure. Keep bottle tightened to keep product fresh and effective. Adults and children 2 years old and older. Use to clean minor cuts, scrapes and burns by thoroughly washing with water. Rinse and air dry. Use no more than 3 times a day.
- Children under two years of age, ask a doctor

RECENT MAJOR CHANGES

Directions for Use were added.

WARNINGS

For external use only

- avoid contact with eyes
- do not exceed recommended dosage unless directed by a doctor

Do not use

- in the eyes or apply to large areas of body
- longer than 1 week unless directed by a doctor
- in large quantities particularly over raw surfaces or blistered areas
- ask a doctor before use if you have deep or puncture wounds, animal bites, or serious burns

Stop Use and ask a doctor if

- condition worsens or symptoms persist for more than 7 days or clear up and occur again within a few days.

INACTIVE INGREDIENT

Inactive Ingredients: Allantoin, Aloe Barbadensis (Aloe) Powder, Arnica Montana (Arnica) Extract, Caprylyl Glycol, Cocoamidopropyl Betaine, Deionized Water, Disdoium Cocoamphodiacetate, Glycerin, Hexylene Glycol, Phenoxyethanol, Sodium Chloride.

Keep out of reach of children:

If swallowed, get medical help or contact a Poison Control Center right away.

Questions? 574-975-3632

Active Ingredient

Lidocaine HCL 4%

Purpose

Topical anesthetic

First aid antiseptic

STATEMENT OF IDENTITY

ELECTRUM NUMB FOAM FOAMING ANESTHETIC

Directions

Shake well before each use. Apply 2 to 3 pumps of foam soap and gently rub into skin. Leave it on for 5 to 10 minutes.

Rinse off gently with running water or wipe with a clean paper towel. Use before, during and after the procedure.